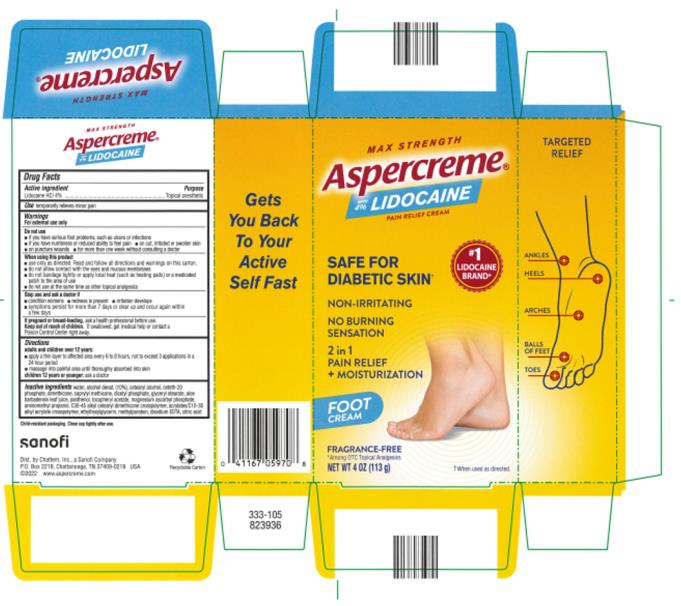 DRUG LABEL: Aspercreme Lidocaine Foot (Diabetic)
NDC: 41167-0597 | Form: CREAM
Manufacturer: Chattem, Inc.
Category: otc | Type: HUMAN OTC DRUG LABEL
Date: 20231023

ACTIVE INGREDIENTS: LIDOCAINE HYDROCHLORIDE 4 g/100 g
INACTIVE INGREDIENTS: WATER; ALCOHOL; CETOSTEARYL ALCOHOL; CETETH-20 PHOSPHATE; DIMETHICONE; CAPRYLYL TRISILOXANE; DIHEXADECYL PHOSPHATE; GLYCERYL MONOSTEARATE; ALOE VERA LEAF; PANTHENOL; .ALPHA.-TOCOPHEROL ACETATE; MAGNESIUM ASCORBYL PHOSPHATE; AMINOMETHYLPROPANOL; C30-45 ALKYL CETEARYL DIMETHICONE CROSSPOLYMER; ETHYLHEXYLGLYCERIN; METHYLPARABEN; EDETATE DISODIUM ANHYDROUS; CITRIC ACID MONOHYDRATE; CARBOMER INTERPOLYMER TYPE A (ALLYL SUCROSE CROSSLINKED)

Aspercreme Lidocaine Foot Cream-Diabetic

ASPERCREME with LIDOCAINE FOOT PAIN CREAM

(For Diabetic Skin)

Drug Facts

Active ingredient

Lidocaine HCl 4%

Purpose

Topical anesthetic

Use

temporarily relieves minor pain

Warnings

For external use only

Do not use

■ if you have serious foot problems, such as ulcers or infections

■ if you have numbness or reduced ability to feel pain

■ on cut, irritated or swollen skin

■on puncture wounds

■ for more than one week without consulting a doctor

When using this product

■ use only as directed. Read and follow all directions and warning on this carton.

■ do not allow contact with the eyes and the mucous membranes

■ do not bandage tightly or apply local heat (such as heating pads) or a medicated patch to the area of use

■ do not use at the same time as other topical analgesics

Stop use and ask a doctor if

■ condition worsens

■ redness is present

■ irritation develops

■ symptoms persist for more than 7 days or clear up and occur again within a few days

If pregnant or breast-feeding,

ask a health professional before use.

Keep out of reach of children.

If swallowed, get medical help or contact a Poison Control Center right away.

Directions

adults and children over 12 years:

■ apply a thin layer to affected area every 6 to 8 hours, not to exceed 3 applications in a 24 hour period

■ massage into painful area until thoroughly absorbed into skin

children 12 years or younger: ask a doctor

Inactive ingredients

water, alcohol denat. (10%), cetearyl alcohol, ceteth-20 phosphate, dimethicone, caprylyl methicone, dicetyl phosphate, glyceryl stearate, aloe barbadensis leaf juice, panthenol, tocopheryl acetate, magnesium ascorbyl phosphate, aminomethyl propanol, C30-45 alkyl cetearyl dimethicone crosspolymer, acrylates/C10-30 alkyl acrylate crosspolymer, ethylhexylglycerin, methylparaben, disodium EDTA, citric acid

333-105

Child-resistant packaging. Close cap tightly after use.

PRINCIPAL DISPLAY PANEL

Max Strength
Aspercreme
Lidocaine
2 in 1
Pain Relief + Moisturization
foot cream